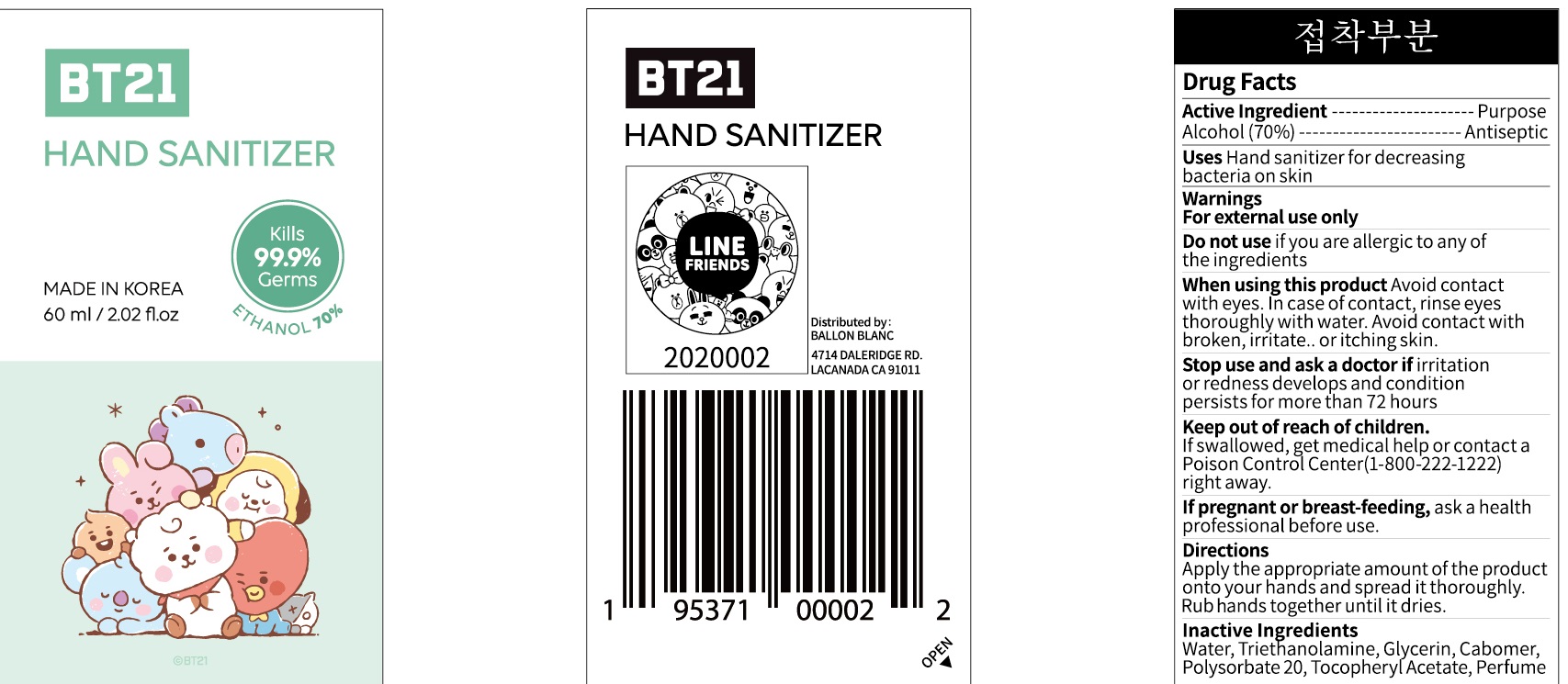 DRUG LABEL: BT21 HAND SANITIZER
NDC: 78967-020 | Form: GEL
Manufacturer: BALLON BLANC
Category: otc | Type: HUMAN OTC DRUG LABEL
Date: 20200922

ACTIVE INGREDIENTS: ALCOHOL 42 mL/60 mL
INACTIVE INGREDIENTS: Water; TROLAMINE; Glycerin; CARBOMER HOMOPOLYMER, UNSPECIFIED TYPE; Polysorbate 20; .ALPHA.-TOCOPHEROL ACETATE

ACTIVE INGREDIENT

Alcohol (70%)

INACTIVE INGREDIENTS

Water, Triethanolamine, Glycerin, Carbomer, Polysorbate 20, Tocopheryl Acetate, Perfume

PURPOSE

Antiseptic

WARNINGS

For external use only
Do not use if you are allergic to any of the ingredients
When using this product Avoid contact with eyes. in case of contact, rinse eyes thoroughly with water. Avoid contact with broken, irritate. or itching skin.
Stop use and ask a doctor if irritation or redness develops and condition persists for more than 72 hours.
Keep out of reach of children. if swallowed, get medical help or contact a Poison Control Center(1-800-222-1222) right away.
If pregnant or brest-feeding, ask a health professional before use.

Keep out of reach of children. if swallowed, get medical help or contact a Poison Control Center(1-800-222-1222) right away.

Uses

Hand sanitizer for decreasing bacteria on skin

Directions

Apply the appropriate amount of the product onto your hands and spread it thoroughly.

Rub hands together until it dries.